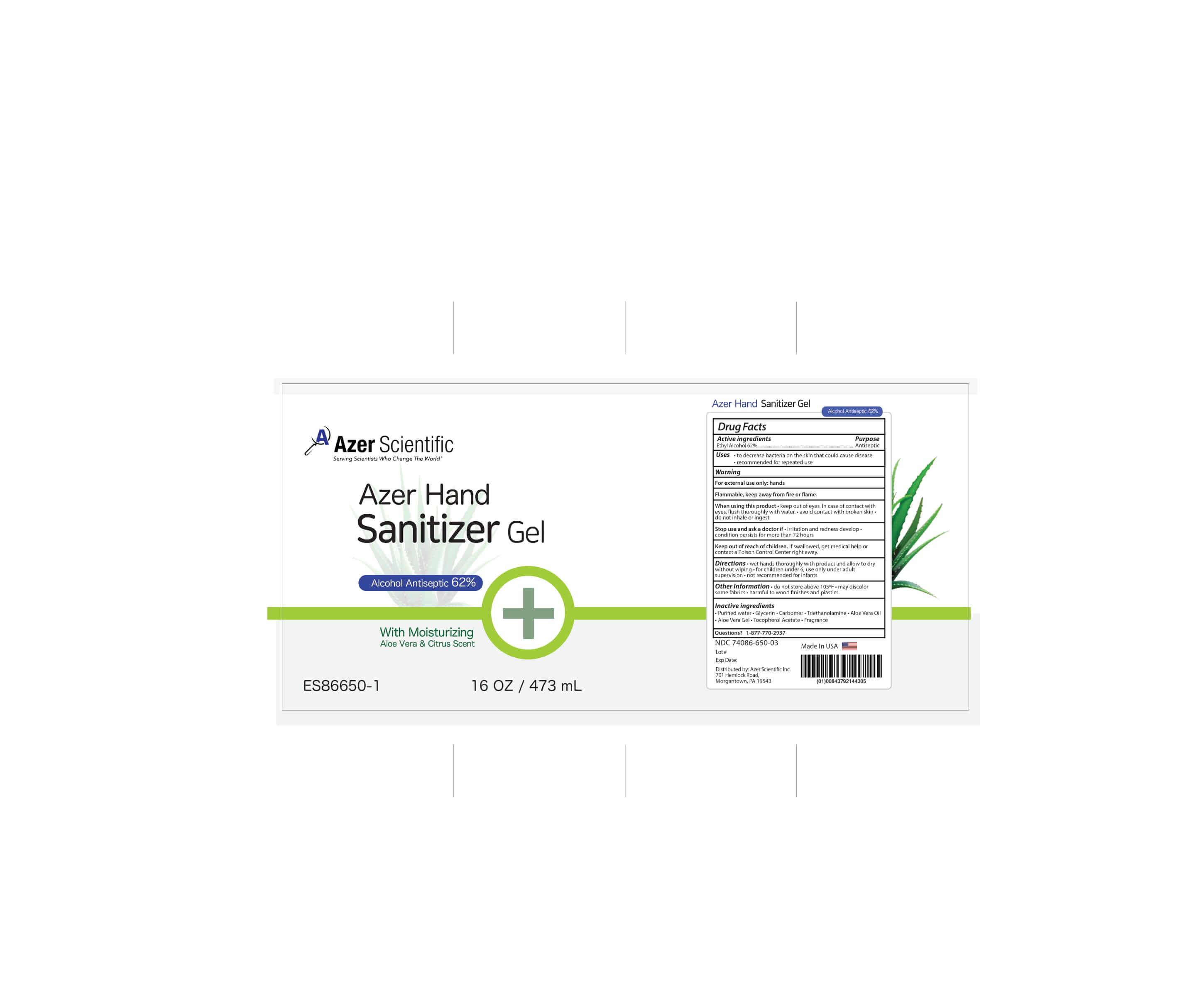 DRUG LABEL: Azer Hand Sanitizer
NDC: 74086-650 | Form: GEL
Manufacturer: Azer Scientific, Inc.
Category: otc | Type: HUMAN OTC DRUG LABEL
Date: 20200417

ACTIVE INGREDIENTS: ALCOHOL 62 mL/100 mL
INACTIVE INGREDIENTS: ALOE VERA LEAF; .ALPHA.-TOCOPHEROL ACETATE; CARBOMER 940; GLYCERIN; WATER; TROLAMINE

Azer Hand Sanitizer

Purpose

Antiseptic

Uses

- to decrease bacteria on the skin that could cause disease
- recommended for repeated use

Warning

For external use only: hands

Flammable, keep away from fire or flame

When using this product, keep out of eyes. In case of contact with eyes, flush throughly with water. Avoid contact with broken skin. Do not inhale or ingest

Stop use and ask a doctor if

- Irritation and redness develop
- Condition persists for more than 72 hours

Keep out of reach of children

If swallowed, get medical help or contact a Poison Control Center right away.

Directions

- Wet hands thoroughly with product and allow to dry without wiping.
- For children under 6, use only under adult supervision.
- Not recommended for infants

Dosage and administration changes

Change from COVID template to match current labeling

Other Information

- Do not store above 105°F
- May discolor some fabrics
- Harmful to wood finishes and plastics

Inactive ingredients

• Purified water • Glycerin • Carbomer • Triethanolamine • Aloe Vera Oil
• Aloe Vera gel • Tocopherol Acetate • Fragrance

Questions?

1-877-770-2937

Package Label - Principal Display Panel

Azer Hand

Sanitizer Gel

Alcohol Antiseptic 62%

With Moisturizing

Aloe Vera & Citrus Scent

16 fl. oz. (473 mL) NDC: 74086-650-02